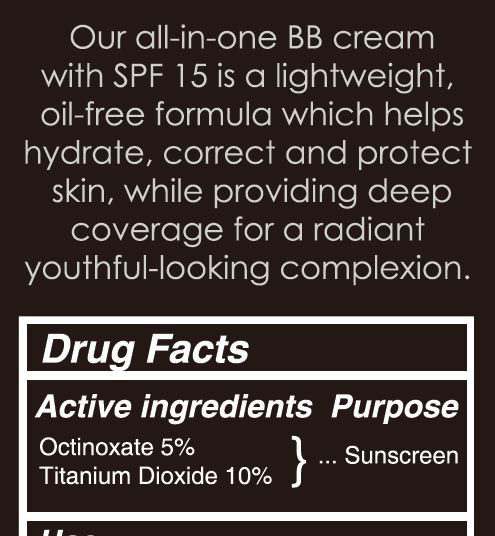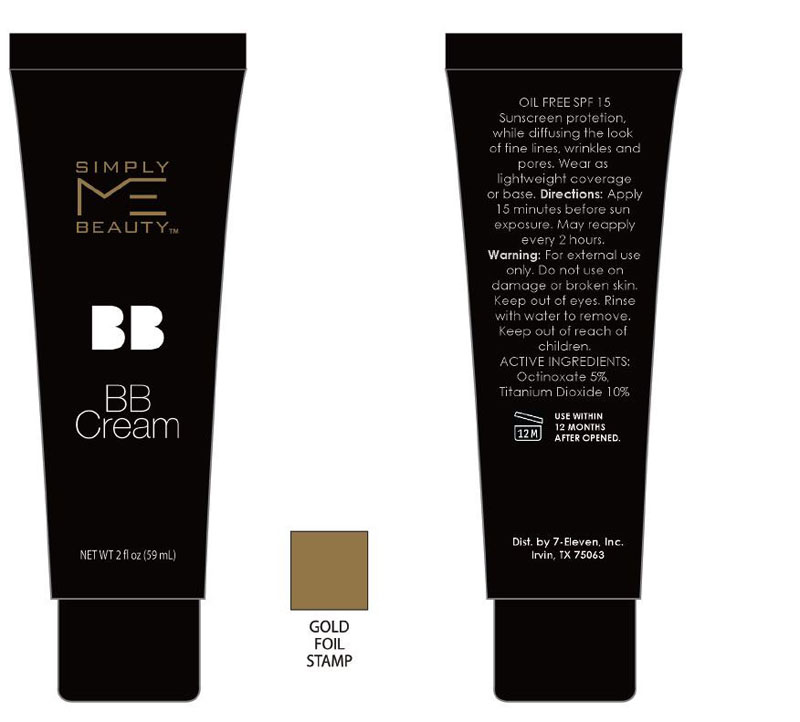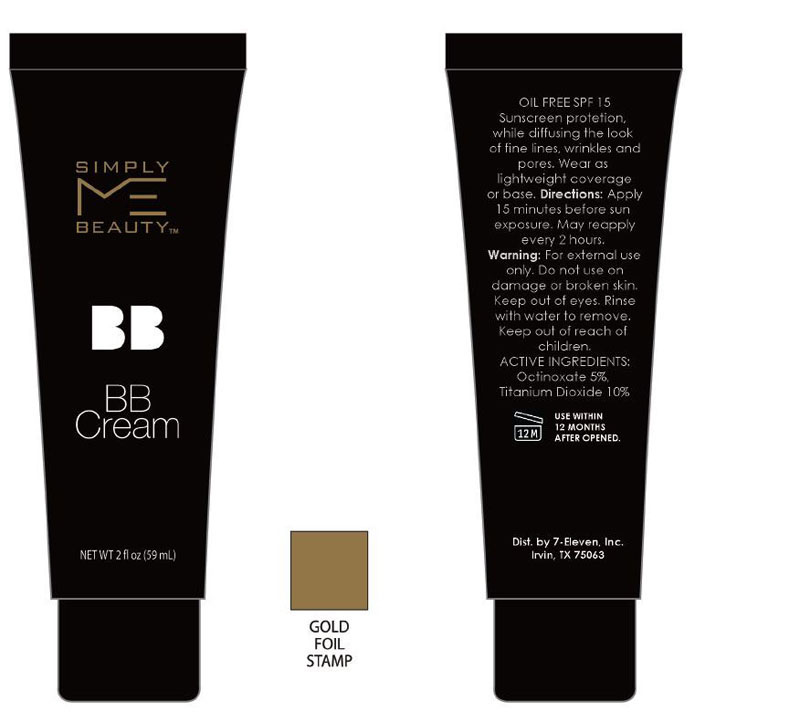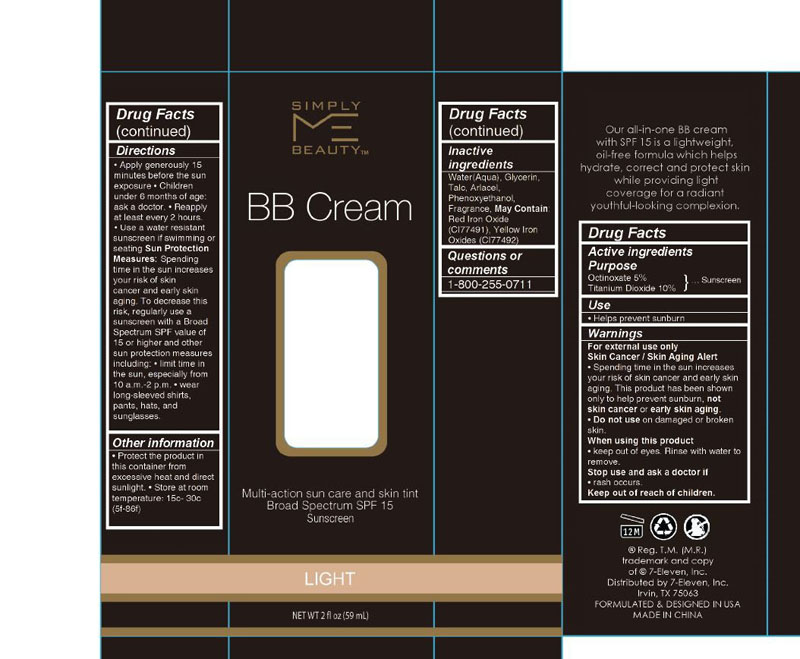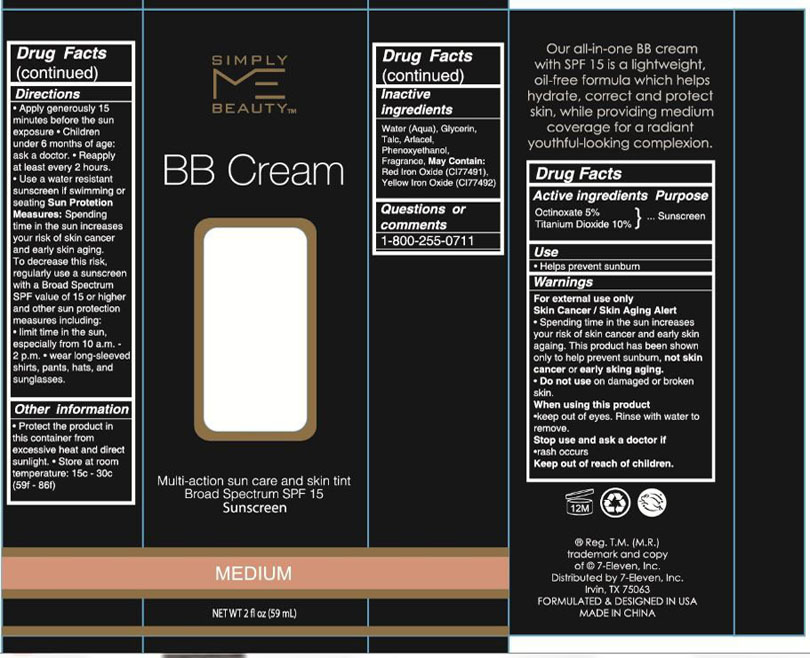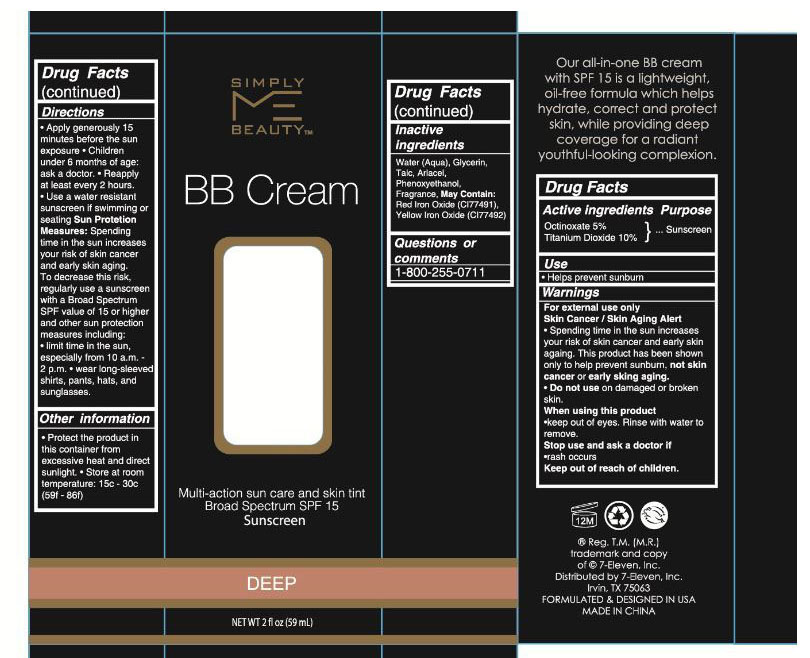 DRUG LABEL: Simply Me Beauty Foundation Cream Light - SPF 15
NDC: 71797-222 | Form: LIQUID
Manufacturer: Beauty Sourcing, LLC
Category: otc | Type: HUMAN OTC DRUG LABEL
Date: 20181128

ACTIVE INGREDIENTS: OCTINOXATE 2.9 g/59 mL; TITANIUM DIOXIDE 5.9 g/59 mL
INACTIVE INGREDIENTS: SORBITAN SESQUIOLEATE 3.54 mL/59 mL; PHENOXYETHANOL 0.295 mL/59 mL; ABRONIA FRAGRANS FLOWER 0.118 mL/59 mL; GLYCERIN 7.08 mL/59 mL; TALC 5.9 mL/59 mL; WATER 30.27 mL/59 mL

BB Cream with SPF 15 - Sunscreen, Drug Fact

BB Cream with Spf 15 - Sunscreen. Drug Fact - Active Ingredient

BB Cream with Spf 15 - Sunscreen. Drug Fact - Purpose and Use of Active Ingredients

Purpose: Sunscreen

Use: Helps prevent sunburn.

BB Cream with Spf 15 - Sunscreen. Drug Fact - Warning Section

For external use only

Skin Cancer / Skin Aging Alert

• Spending time in the sun increases your risk of skin cancer and early skin aging. This product has been shown only to help prevent sunburn, not skin cancer or early skin aging.

• Do not use on damaged or broken skin.

When using this product

• keep out of eyes. Rinse with water to remove.

Stop use and ask a doctor if

• rash occurs.

Keep out of reach of children.

BB Cream with Spf 15 - Sunscreen. Drug Fact - Warning - Ask Doctor if

Stop use and ask a doctor if

• rash occurs.

BB Cream with Spf 15 - Sunscreen. Drug Fact - Warning - DO Not Use

Do not use on damaged or broken skin.

When using this product • keep out of eyes. Rinse with water to remove.

BB Cream with Spf 15 - Sunscreen. Drug Fact - Warnings - Stop Use

Stop use and ask a doctor if • rash occurs.

BB Cream with Spf 15 - Sunscreen. Drug Fact - Warnings - Keep out Reach

Keep out of reach of children is visible in the Warnings box of packaging.

Keep out of reach of children.

BB Cream with Spf 15 - Sunscreen. Drug Fact - Warnings - When Using

When Using this product • Keep out of eyes. Rinse with water to remove.

BB Cream with Spf 15 - Sunscreen. Drug Fact - Directions

Indications & Usage section is illustrated in the Directions section.

• Apply generously 15 minutes before the sun exposure • Children under 6 months of age: ask a doctor. • Reapply at least every 2 hours.• Use a water-resistant sunscreen if swimming or seating. Sun Protection Measures: Spending time in the sun increases your risk of skin cancer and early skin aging. To decrease this risk, regularly use a sunscreen with a Broad Spectrum SPF value of 15 or higher and other sun protection measures including: • limit time in the sun, especially from 10 a.m.-2 p.m. • wear long-sleeved shirts, pants, hats, and sunglasses .

BB Cream with Spf 15 - Sunscreen. Drug Fact - Directions - Dosage and Admin

BB cream Foundation with Sunscreen is a topical liquid. Apply generously 15 minutes before the sun exposure. May reapply at least every 2 hours.

BB Cream with Spf 15 - Sunscreen. Drug Fact - Other informaton

Other information. • Protect the product in this container from excessive heat and direct sunlight. • Store at room temperature: 15c - 30c (59f-86f).

BB Cream with Spf 15 - Sunscreen. Drug Fact - Inactive ingredients

BB cream with Spf 15 Inactive ingredients include:

Water(Aqua), Glycerin, Talc, Arlacel, Phenoxyethanol, Fragrance, May Contain: Red Iron Oxide (CI77491), Yellow Iron Oxides (CI77492)

BB Cream with Spf 15 - Sunscreen. Drug Fact - Questions Section

Question or Comments 1-800-255-0711

BB Cream Medium with Spf 15 - Sunscreen. Drug Fact section - packagingouter2 label

packagingouter2

BB Cream Deep with Spf 15 - Sunscreen. Drug Fact section - packagingouter3 packagingInner3 label

packagingouter3.jpg

packagingInner3.jpg